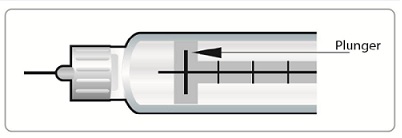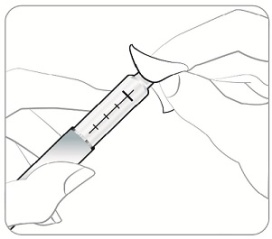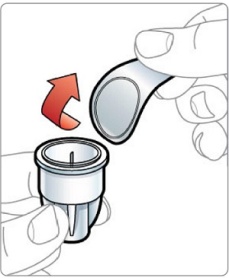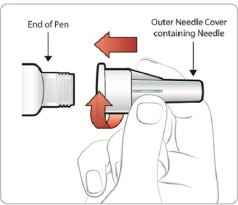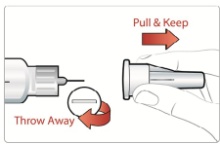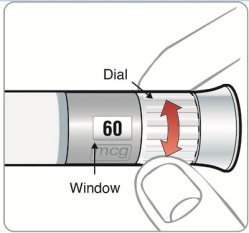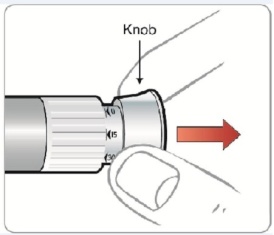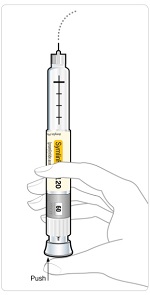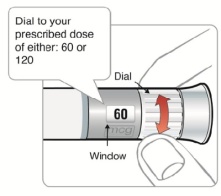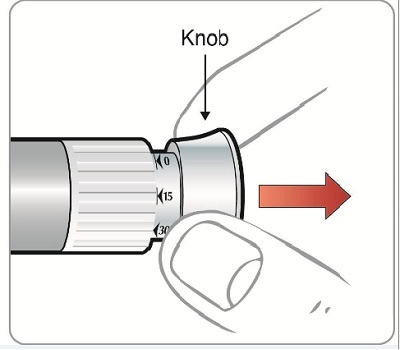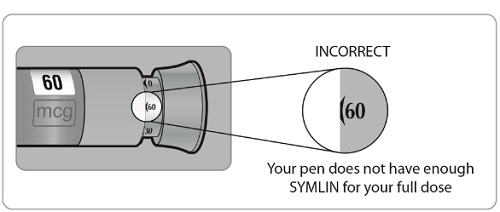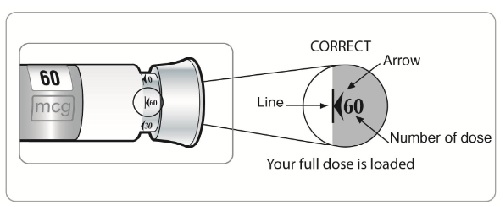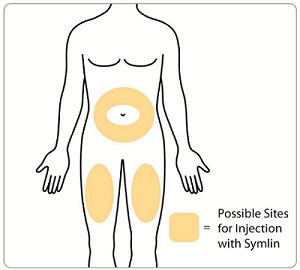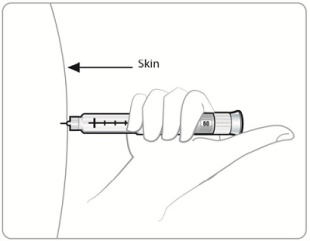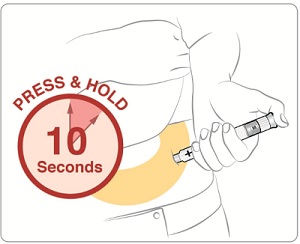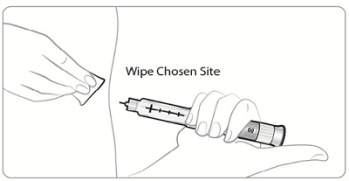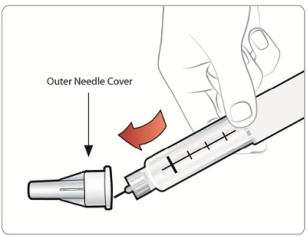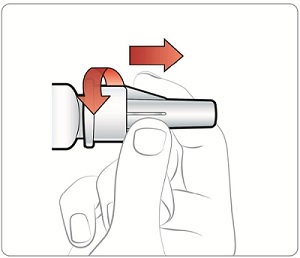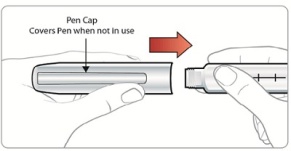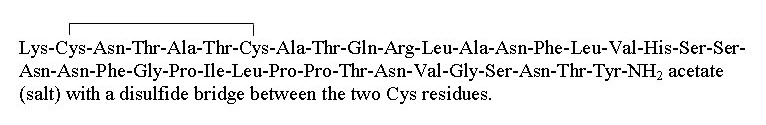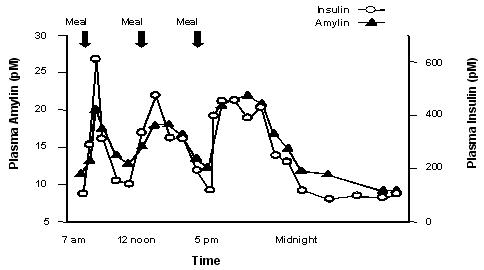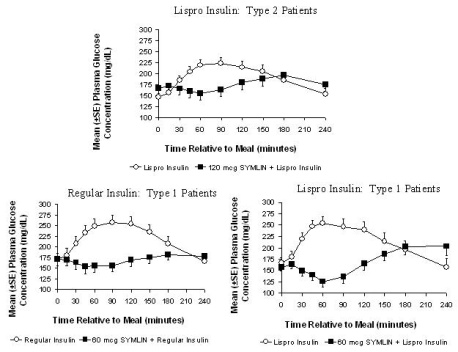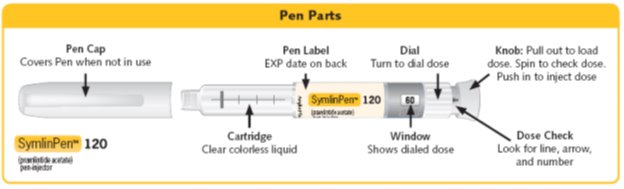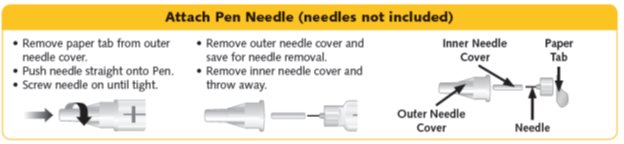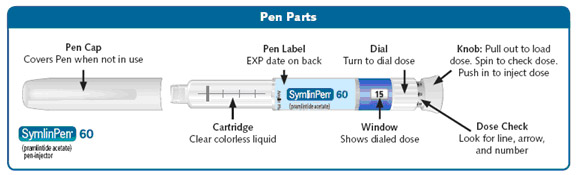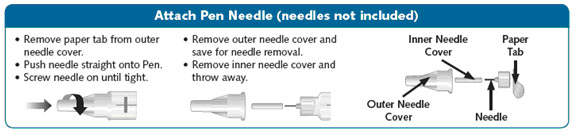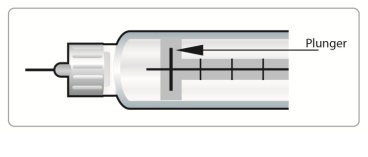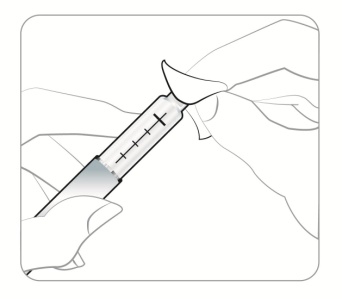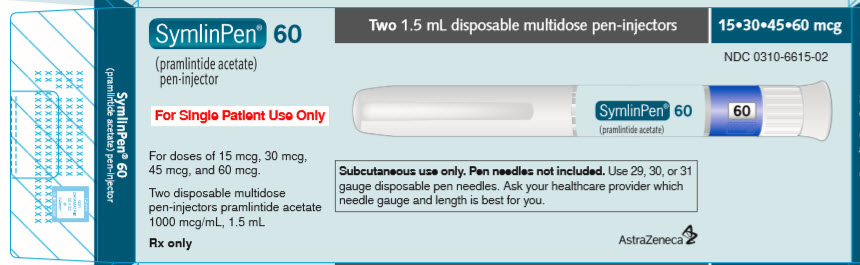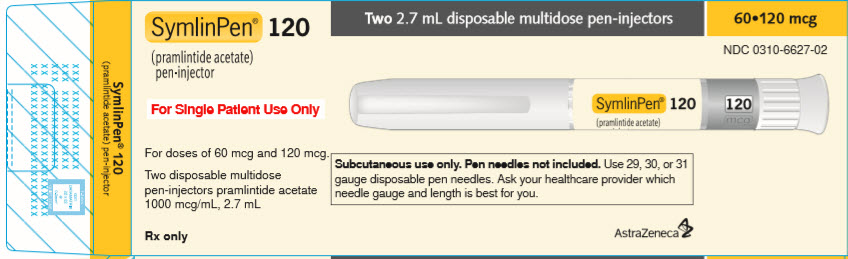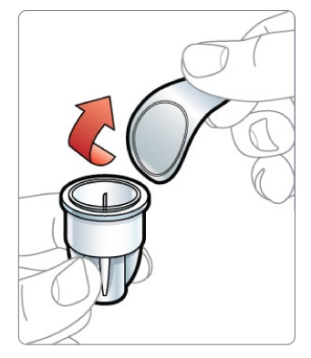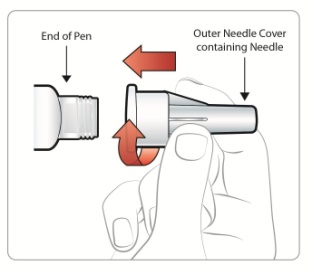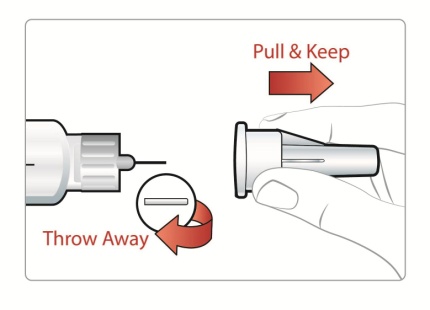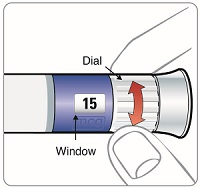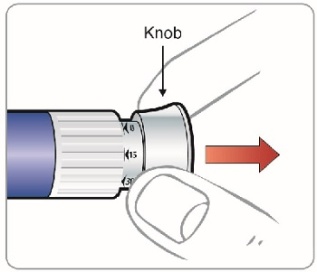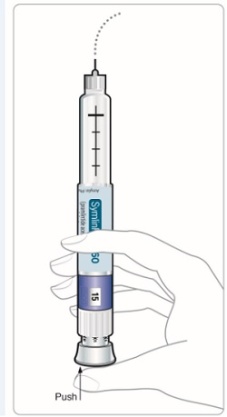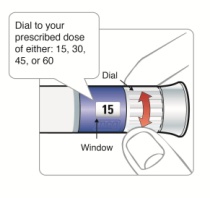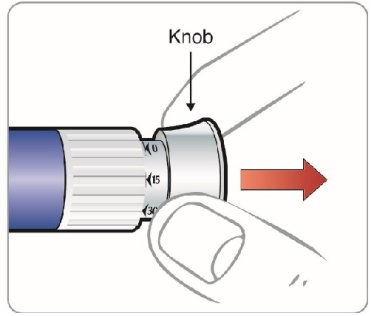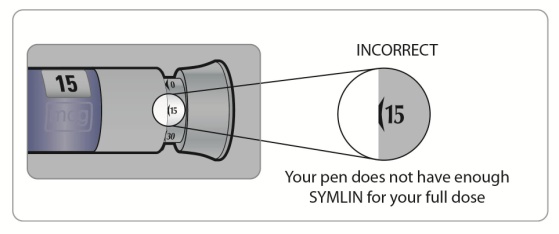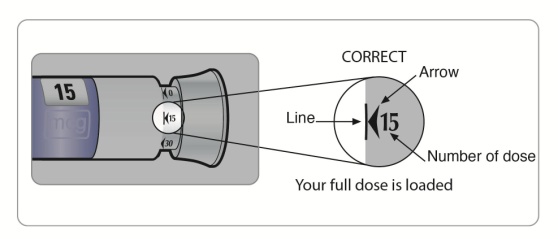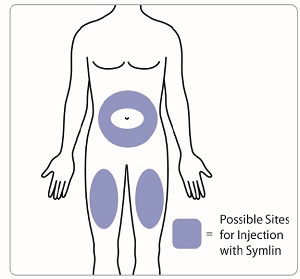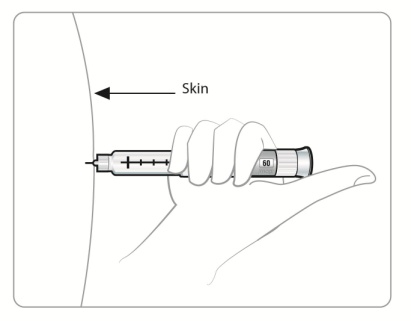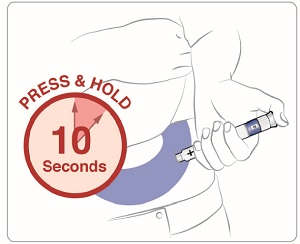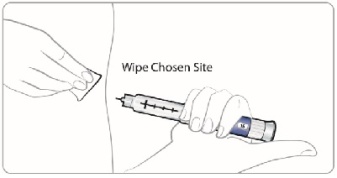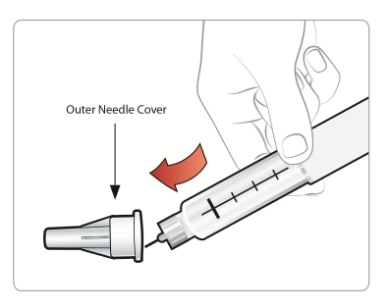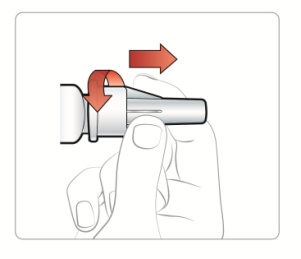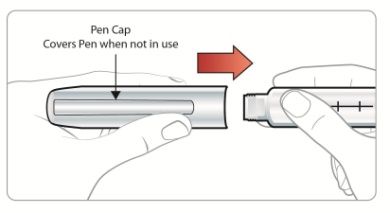 DRUG LABEL: SymlinPen
NDC: 0310-6615 | Form: INJECTION
Manufacturer: AstraZeneca Pharmaceuticals LP
Category: prescription | Type: HUMAN PRESCRIPTION DRUG LABEL
Date: 20191218

ACTIVE INGREDIENTS: pramlintide acetate 1000 ug/1 mL
INACTIVE INGREDIENTS: acetic acid; mannitol; metacresol 2.25 mg/1 mL; sodium acetate; water

HIGHLIGHTS OF PRESCRIBING INFORMATION

These highlights do not include all the information needed to use SYMLIN safely and effectively. See full prescribing information for SYMLIN.
SYMLIN® (pramlintide acetate) injection for subcutaneous use
Initial U.S. Approval: 2005

WARNING: SEVERE HYPOGLYCEMIA

See full prescribing information for complete boxed warning.

- SYMLIN use with insulin has been associated with an increased risk of severe hypoglycemia, particularly in patients with type 1 diabetes.
- Hypoglycemia risk may be reduced by appropriate patient selection, careful patient instruction, and insulin dose reduction (5.1, 5.2).

1 INDICATIONS AND USAGE

SYMLIN is an amylin analog indicated for patients with type 1 or type 2 diabetes who use mealtime insulin and have failed to achieve desired glycemic control despite optimal insulin therapy (1).

2 DOSAGE AND ADMINISTRATION

- Upon initiation of SYMLIN, reduce mealtime insulin dose by 50%. Monitor glucoses frequently and individualize subsequent insulin dose adjustments (2.1).
- Type 1 Diabetes: Start at 15 mcg subcutaneously before major meals. Increase in 15 mcg increments to a maximum premeal dose of 30 or 60 mcg; if not tolerated, reduce to 30 mcg, as tolerated (2.2).
- Type 2 Diabetes: Start at 60 mcg subcutaneously before major meals then increase to 120 mcg before meals, as tolerated (2.2).
- Wait at least 3 days between dose titrations to minimize nausea (2.1).

3 DOSAGE FORMS AND STRENGTHS

- 1.5 mL SymlinPen® 60 disposable multidose pen-injector, (1000 mcg/mL) for 15, 30, 45, and 60 mcg doses (3).
- 2.7 mL SymlinPen® 120 disposable multidose pen-injector, (1000 mcg/mL) for 60 and 120 mcg doses (3).

4 CONTRAINDICATIONS

- Prior serious hypersensitivity reaction to SYMLIN or its ingredients (4)
- Hypoglycemia unawareness (4)
- Confirmed gastroparesis (4)

5 WARNINGS AND PRECAUTIONS

- Severe hypoglycemia: Increased risk particularly for type 1 diabetes. Upon initiation of SYMLIN, reduce mealtime insulin dose by 50% and frequently monitor blood glucoses (5.2).
- Never share a SymlinPen between patients, even if the needle is changed (5.3).
- Do not mix SYMLIN and insulin: Mixing can alter the pharmacokinetics of both products. Administer as separate injections (5.4, 7.1).
- Slows gastric emptying: Administer concomitant oral medications at least 1 hour before or 2 hours after SYMLIN if rapid onset or threshold concentration is critical (5.6, 7.2).

6 ADVERSE REACTIONS

- Most common adverse reactions (incidence ≥5% and higher incidence than placebo): nausea, vomiting, anorexia, headache (6.1).

To report SUSPECTED ADVERSE REACTIONS, contact AstraZeneca at 1-800-236-9933 or FDA at 1-800-FDA-1088 or www.fda.gov/medwatch.

FULL PRESCRIBING INFORMATION

WARNING: SEVERE HYPOGLYCEMIA

SYMLIN use with insulin increases the risk of severe hypoglycemia, particularly in patients with type 1 diabetes. When severe hypoglycemia occurs, it is seen within 3 hours following a SYMLIN injection. Serious injuries may occur if severe hypoglycemia occurs while operating a motor vehicle, heavy machinery, or while engaging in other high-risk activities. Appropriate patient selection, careful patient instruction, and insulin dose reduction are critical elements for reducing this risk.

1 INDICATIONS AND USAGE

SYMLIN is indicated as an adjunctive treatment in patients with type 1 or type 2 diabetes who use mealtime insulin therapy and who have failed to achieve desired glucose control despite optimal insulin therapy.

2 DOSAGE AND ADMINISTRATION

2.1 Important Considerations Pertaining to SYMLIN and Insulin Dose Adjustments

SYMLIN dosage differs depending on whether the patient has type 1 or type 2 diabetes [see Dosage and Administration (2.2, 2.3)].

SYMLIN should be used only in patients who can fully understand and adhere to proper insulin adjustments and glucose monitoring.

Insulin and SYMLIN dose adjustments should be made only as directed by a healthcare professional skilled in the use of insulin.

When initiating SYMLIN, reduce mealtime insulin doses, including premixed insulins, by 50% to reduce the risk of hypoglycemia.

To reduce the risk of nausea, wait at least 3 days before titrating SYMLIN to the next dose increment.

Monitor blood glucoses frequently, including pre- and post-meals and at bedtime, particularly when initiating SYMLIN or increasing the SYMLIN dose. After the initial 50% reduction in mealtime insulin dose, individualize insulin dose adjustments based on glycemic control and tolerability (e.g., if nausea occurs it may affect the dose of insulin required). An increased frequency of mild-to-moderate hypoglycemia should be viewed as a warning sign of increased risk for severe hypoglycemia.

If SYMLIN therapy is discontinued for any reason (e.g., surgery or illnesses), the same initiation protocol should be followed when SYMLIN therapy is reinstituted [see Dosage and Administration (2.2)].

2.2 Patients with Type 2 Diabetes Using Mealtime Insulin

Reduce mealtime insulin doses (including premixed insulins) by 50%, then initiate SYMLIN at 60 mcg subcutaneously, injecting immediately prior to each major meal.

Increase the SYMLIN dose from 60 to 120 mcg prior to each major meal when no clinically significant nausea has occurred for at least 3 days.

If significant nausea persists at the 120 mcg dose, the SYMLIN dose should be decreased to 60 mcg.

2.3 Patients with Type 1 Diabetes

Reduce mealtime insulin doses by 50%, then initiate SYMLIN at 15 mcg subcutaneously, injecting immediately prior to each major meal.

Increase the SYMLIN dose to the next increment (30, 45, or 60 mcg) when no clinically significant nausea has occurred for at least 3 days.

If significant nausea persists at the 45 or 60 mcg dose level, the SYMLIN dose should be decreased to 30 mcg. If the 30 mcg dose is not tolerated, discontinuation of SYMLIN therapy should be considered.

2.4 Administration

SYMLIN should be administered subcutaneously immediately prior to each major meal (≥250 kcal or containing ≥30 grams of carbohydrate).

SYMLIN should be at room temperature before injecting to reduce potential injection site reactions. Each SYMLIN dose should be administered subcutaneously into the abdomen or thigh. Administration into the arm is not recommended because of variable absorption. Injection sites should be rotated so that the same site is not used repeatedly. The injection site selected should also be distinct from the site chosen for any concomitant insulin injection.

SYMLIN and insulin should always be administered as separate injections.

SYMLIN should not be mixed with any type of insulin.

If a SYMLIN dose is missed, wait until the next scheduled dose and administer the usual amount.

2.5 Discontinuation of Therapy

SYMLIN therapy should be discontinued if there is:

- recurrent unexplained hypoglycemia that requires medical assistance.
- persistent clinically significant nausea.
- noncompliance with self-monitoring of blood glucose concentrations.
- noncompliance with insulin dose adjustments.
- noncompliance with scheduled healthcare provider contacts or recommended clinic visits.

2.6 Preparation and Handling

SYMLIN should be inspected visually for particulate matter or discoloration prior to administration whenever the solution and the container permit.

3 DOSAGE FORMS AND STRENGTHS

SYMLIN is supplied as a sterile injection in the following dosage forms:

- 1.5 mL disposable multidose SymlinPen® 60 pen-injector containing 1000 mcg/mL pramlintide (as acetate).
- 2.7 mL disposable multidose SymlinPen® 120 pen-injector containing 1000 mcg/mL pramlintide (as acetate).

4 CONTRAINDICATIONS

SYMLIN is contraindicated in patients with any of the following:

- serious hypersensitivity reaction to SYMLIN or to any of its product components.
- hypoglycemia unawareness.
- confirmed gastroparesis.

5 WARNINGS AND PRECAUTIONS

5.1 Patient Selection

Proper patient selection is critical to the safe and effective use of SYMLIN. Before initiating SYMLIN, the patient's HbA1c, recent blood glucose monitoring data, history of insulin-induced hypoglycemia, current insulin regimen, and body weight should be reviewed. SYMLIN therapy should only be considered in patients with type 1 diabetes or patients with type 2 diabetes using mealtime insulin who fulfill the following criteria:

- have failed to achieve adequate glycemic control despite individualized insulin management.
- are receiving ongoing care under the guidance of a healthcare professional skilled in the use of insulin and supported by the services of diabetes educator(s).

Patients meeting any of the following criteria should NOT be considered for SYMLIN therapy:

- poor compliance with current insulin regimen.
- poor compliance with prescribed self blood glucose monitoring.
- have a HbA1c >9%.
- recurrent severe hypoglycemia requiring assistance during the past 6 months.
- presence of hypoglycemia unawareness.
- confirmed diagnosis of gastroparesis.
- require the use of drugs that stimulate gastrointestinal motility.
- pediatric patients.

SYMLIN should be prescribed with caution to persons with visual or dexterity impairment.

5.2 Hypoglycemia

SYMLIN alone does not cause hypoglycemia. However, SYMLIN is indicated to be coadministered with mealtime insulin therapy, and in this setting there is an increased risk of severe hypoglycemia, particularly in patients with type 1 diabetes. If severe hypoglycemia associated with SYMLIN occurs, it is usually seen within the first 2 to 3 hours following a SYMLIN injection. If severe hypoglycemia occurs while operating a motor vehicle, heavy machinery, or while engaging in other high-risk activities, serious injuries or death may occur. Therefore, when introducing SYMLIN therapy, appropriate precautions need to be taken to avoid increasing the risk for severe hypoglycemia. These precautions include frequent monitoring of pre- and post-meal glucose combined with an initial 50% reduction in doses of mealtime insulin [see Dosage and Administration (2.1, 2.2)].

Early warning symptoms of hypoglycemia may be different or less pronounced under certain conditions, such as longstanding diabetes; diabetic neuropathy; use of medications such as beta-blockers, clonidine, guanethidine, or reserpine; or intensified glycemic control.

The addition of any anti-diabetic medication, such as SYMLIN, to an existing regimen of one or more anti-diabetic medications (e.g., sulfonylurea), or other medications that can increase the risk of hypoglycemia may necessitate further insulin dose adjustments and particularly close monitoring of blood glucose.

5.3 Never Share a SymlinPen Between Patients

SymlinPen must never be shared between patients, even if the needle is changed. Pen-sharing poses a risk for transmission of blood-borne pathogens.

5.4 Never Mix SYMLIN and Insulin

Mixing SYMLIN and insulin can alter the pharmacokinetics of both products which may result in inadequate glucose control or hypoglycemia. Therefore, SYMLIN and insulin must always be administered as separate injections and should never be mixed [see Drug Interactions (7.1) and Clinical Pharmacology (12.3)].

5.5 Concomitantly Administered Oral Medications

SYMLIN slows gastric emptying, which may delay the absorption of concomitantly administered oral medications. Administer the concomitant oral medication at least 1 hour prior to SYMLIN injection or 2 hours after SYMLIN injection if the rapid onset or threshold concentration of the concomitant medication is a critical determinant of its effectiveness (such as with analgesics, antibiotics, and oral contraceptives) [see Drug Interactions (7.2) and Clinical Pharmacology (12.3)].

5.6 Medications that Affect Gastrointestinal Motility

SYMLIN slows gastric emptying. SYMLIN is not recommended for patients taking other medications that alter gastrointestinal motility [see Drug Interactions (7.3)].

5.7 Allergy

Local Allergy

Patients may experience erythema, edema, or pruritus at the site of injection. These minor reactions usually resolve in a few days to a few weeks. In some instances, these reactions may be related to factors other than SYMLIN, such as irritants in a skin cleansing agent or improper injection technique.

6 ADVERSE REACTIONS

Because clinical trials are conducted under widely varying conditions, adverse reaction rates observed in the clinical trials of a drug cannot be directly compared to rates in the clinical trials of another drug and may not reflect the rates observed in practice.

6.1 Clinical Trial Experience

Adverse reactions (excluding hypoglycemia, which is discussed separately below) commonly associated with SYMLIN when coadministered with a fixed dose of insulin in the 26- to 52-week, placebo-controlled trials in patients with type 1 diabetes and patients with type 2 diabetes on mealtime insulin are presented in Table 1 and Table 2, respectively.

Table 1: Patients with Type 1 Diabetes: Common Adverse Reactions (Incidence ≥5% and Greater Incidence with SYMLIN Compared to Placebo) in 3 Pooled Placebo-Controlled Trials
 | Long-Term, Placebo-Controlled Studies
 | SYMLIN 30 or 60 mcg 3 Times Daily + Insulin | Placebo + Insulin
 | (N=716) % | (N=538) %
Nausea | 48 | 17
Anorexia | 17 | 2
Inflicted Injury [Examples of inflicted injury included among others, abrasions, bruises, burns, fractures, lacerations, and muscle strains.] | 14 | 10
Vomiting | 11 | 7
Arthralgia | 7 | 5
Fatigue | 7 | 4
Allergic Reaction | 6 | 5
Dizziness | 5 | 4

Table 2: Patients with Type 2 Diabetes on Insulin: Common Adverse Reactions (Incidence ≥5% and Greater Incidence with SYMLIN Compared to Placebo) in 2 Pooled Placebo-Controlled Trials
 | Long-Term, Placebo-Controlled Studies
 | SYMLIN 120 mcg 2 Times Daily + Insulin | Placebo + Insulin
 | (N=292) % | (N=284) %
Nausea | 28 | 12
Headache | 13 | 7
Anorexia | 9 | 2
Vomiting | 8 | 4
Abdominal pain | 8 | 7
Fatigue | 7 | 4
Dizziness | 6 | 4
Cough | 6 | 4
Pharyngitis | 5 | 2

Most adverse reactions were gastrointestinal in nature. The incidence of nausea is higher at the beginning of SYMLIN treatment and decreases with time in most patients. Gradual titration of the SYMLIN dose minimizes the incidence and severity of nausea [see Dosage and Administration (2)].

Severe Hypoglycemia

Coadministration of SYMLIN with mealtime insulin increases the risk of severe hypoglycemia, particularly in patients with type 1 diabetes [see Boxed Warning and Warnings and Precautions (5.1)].

Two definitions of severe hypoglycemia were used in the SYMLIN clinical trials. Patient-ascertained severe hypoglycemia was defined as an episode of hypoglycemia requiring the assistance of another individual (including help administering oral carbohydrate) or requiring the administration of glucagon, intravenous glucose, or other medical intervention. Medically-assisted severe hypoglycemia was defined as an episode of hypoglycemia that was classified as a serious event by the investigator or that required glucagon, intravenous glucose, hospitalization, paramedic assistance or an emergency room visit. The incidence of severe hypoglycemia during the SYMLIN clinical development program is summarized in Table 3 and Table 4.

Table 3: Incidence and Event Rate of Severe Hypoglycemia in Six-Month, Placebo-Controlled Trials and Dose Titration Trial in Patients with Type 1 Diabetes
 | Long-Term, Placebo-Controlled Studies (No Insulin Dose-Reduction During Initiation) |  |  |  | Placebo-Controlled Dose Titration Study
 | SYMLIN + Insulin |  | Placebo + Insulin |  | SYMLIN + Insulin |  | Placebo + Insulin
Severe Hypoglycemia | 0 to 3 Months (n=716) | >3 to 6 Months (n=576) | 0 to 3 Months (n=538) | >3 to 6 Months (n=470) | 0 to 3 Months (n=148) | >3 to 6 Months (n=133) | 0 to 3 Months (n=147) | >3 to 6 Months (n=138)
Patient-Ascertained [Patient-ascertained severe hypoglycemia: Requiring the assistance of another individual (including help ingesting oral carbohydrate) and/or requiring the administration of glucagon injection, intravenous glucose, or other medical intervention.]
Event Rate (events/patient-year) | 1.55 | 0.82 | 1.33 | 1.06 | 0.69 | 0.49 | 0.28 | 0.3
Subject Incidence (%) | 16.8 | 11.1 | 10.8 | 8.7 | 13.5 | 10.5 | 6.1 | 5.8
Medically-Assisted [Medically-assisted severe hypoglycemia: Requiring glucagon, intravenous glucose, hospitalization, paramedic assistance, emergency room visit, and/or assessed as a serious adverse event by the investigator.]
Event Rate (events/patient-year) | 0.50 | 0.27 | 0.19 | 0.24 | 0.14 | 0.20 | 0.08 | 0.15
Subject Incidence (%) | 7.3 | 5.2 | 3.3 | 4.3 | 3.4 | 4.5 | 2.0 | 2.9

Table 4: Incidence and Event Rate of Severe Hypoglycemia in Six-Month, Placebo-Controlled Trials in Patients with Type 2 Diabetes Using Insulin
 | Long-Term, Placebo-Controlled Studies (No Insulin Dose-Reduction During Initiation)
 | SYMLIN + Insulin |  | Placebo + Insulin
Severe Hypoglycemia | 0 to 3 Months (n=292) | >3 to 6 Months (n=255) | 0 to 3 Months (n=284) | >3 to 6 Months (n=251)
Patient-Ascertained [Patient-ascertained severe hypoglycemia: Requiring the assistance of another individual (including help ingesting oral carbohydrate) and/or requiring the administration of glucagon injection, intravenous glucose, or other medical intervention.]
Event Rate (events/patient-year) | 0.45 | 0.39 | 0.24 | 0.13
Subject Incidence (%) | 8.2 | 4.7 | 2.1 | 2.4
Medically-Assisted [Medically-assisted severe hypoglycemia: Requiring glucagon, intravenous glucose, hospitalization, paramedic assistance, emergency room visit, and/or assessed as a serious adverse event by the investigator.]
Event Rate (events/patient-year) | 0.09 | 0.02 | 0.06 | 0.07
Subject Incidence (%) | 1.7 | 0.4 | 0.7 | 1.2

6.2 Postmarketing Experience

The following adverse reactions have been identified during post-approval use of SYMLIN. Because these reactions are reported voluntarily from a population of uncertain size, it is not always possible to reliably estimate their frequency or establish a causal relationship to drug exposure.

- Injection site reactions
- Pancreatitis

7 DRUG INTERACTIONS

7.1 Insulin

The pharmacokinetic parameters of pramlintide are altered when SYMLIN is mixed in the same syringe with regular, NPH, and 70/30 premixed formulations of recombinant human insulin. SYMLIN and insulin must not be mixed and must be administered as separate injections [see Dosage and Administration (2.4), Warnings and Precautions (5.4), and Clinical Pharmacology (12.3)].

7.2 Oral Medications

SYMLIN has the potential to delay the absorption of concomitantly administered oral medications. When the rapid onset or threshold concentration of a concomitant orally administered medication is a critical determinant of effectiveness (such as with analgesics, antibiotics, and oral contraceptives), the medication should be administered at least 1 hour prior to SYMLIN injection or 2 hours after SYMLIN injection [see Warnings and Precautions (5.5) and Clinical Pharmacology (12.3)].

7.3 Drugs Affecting Gastrointestinal Motility

Due to its effects on gastric emptying, SYMLIN should not be considered for patients taking medications that alter gastrointestinal motility (e.g., anticholinergic agents such as atropine) or medications that slow the intestinal absorption of nutrients (e.g., alpha-glucosidase inhibitors). Patients using these medications have not been studied in SYMLIN clinical trials [see Warnings and Precautions (5.6)].

7.4 Drugs Affecting Glucose Metabolism

The following are examples of medications that may increase the susceptibility to hypoglycemia when administered with SYMLIN: anti-diabetic products, angiotensin converting enzyme (ACE) inhibitors, disopyramide, fibrates, fluoxetine, monoamine oxidase inhibitors, pentoxifylline, salicylates, somatostatin analogs, and sulfonamide antibiotics. SYMLIN and these drugs should be coadministered with caution.

8 USE IN SPECIFIC POPULATIONS

8.1 Pregnancy

Risk Summary

Available data from a small number of reports in the manufacturer’s safety database on SYMLIN use in pregnant women are not sufficient to determine a drug-associated risk for major birth defects, miscarriage, or other adverse maternal or fetal outcomes. There are risks to the mother and fetus associated with poorly controlled diabetes in pregnancy (see Clinical Considerations).

Ex-vivo studies using term perfused human, rabbit, and rat placentas indicate that SYMLIN has low potential to cross the maternal/fetal placental barrier. In animal reproduction studies, congenital abnormalities were observed in fetuses of pregnant rats but not in fetuses of pregnant rabbits exposed during organogenesis to pramlintide at 10 times the clinical dose of 360 mcg/day, based on exposure (see Data).

The estimated background risk of major birth defects is 6-10% in women with pre-gestational diabetes with an HbA1c >7 and has been reported to be as high as 20-25% in women with HbA1c >10. The estimated background risk of miscarriage for the indicated population is unknown. In the U.S. general population, the estimated background risk of major birth defects and miscarriage in clinically recognized pregnancies is 2-4% and 15-20%, respectively.

Clinical Considerations

Disease-associated maternal and/or embryo/fetal risk

Poorly controlled diabetes in pregnancy increases the maternal risk for diabetic ketoacidosis, preeclampsia, spontaneous abortions, preterm delivery, and delivery complications. Poorly controlled diabetes increases the fetal risk for major birth defects, stillbirth, and macrosomia related morbidity.

Data

Animal Data

Developmental and reproductive toxicity studies with SYMLIN were performed in pregnant rats and rabbits. Increases in congenital abnormalities (neural tube defect, cleft palate, exencephaly) were observed in fetuses of pregnant rats administered pramlintide subcutaneously during organogenesis at 0.3 and 1 mg/kg/day (10 and 47 times the human dose of 360 mcg/day based on AUC, respectively), but not at 3mg/kg/day. Administration of pramlintide to pregnant rabbits during organogenesis resulted in maternal toxicity but did not increase fetal malformations at doses up to 0.3 mg/kg/day (9 times the human dose of 360 mcg/day based on AUC).

8.2 Lactation

Risk Summary

There is no data on the presence of pramlintide in human milk, the effects on the breastfed infant, or the effects on milk production. The developmental and health benefits of breastfeeding should be considered along with the mother’s clinical need for SYMLIN and any potential adverse effects on the breastfed child from SYMLIN or from the underlying maternal condition.

8.4 Pediatric Use

Safety and effectiveness of SYMLIN in pediatric patients have not been established.

8.5 Geriatric Use

SYMLIN has been studied in patients ranging in age from 15 to 84 years of age, including 769 patients ≥65 to 75 years of age and 87 patients ≥75 years of age. No consistent differences in the efficacy and safety of SYMLIN have been observed in older patients, but greater sensitivity in some older individuals cannot be ruled out. As is recommended for all patients, SYMLIN and insulin regimens should be carefully managed to minimize the risk of severe hypoglycemia.

8.6 Renal Impairment

The dosing requirements for SYMLIN are not altered in patients with mild (creatinine clearance [ClCr] 60-89 mL/min), moderate (ClCr 30-59 mL/min) or severe renal impairment (ClCr 15-29 mL/min). SYMLIN has not been studied in patients with end-stage renal disease [see Clinical Pharmacology (12.3)].

8.7 Hepatic Impairment

SYMLIN use has not been studied in patients with hepatic impairment [see Clinical Pharmacology (12.3)].

8.8 Gender

No consistent differences in the efficacy and safety of SYMLIN have been observed between men and women in SYMLIN clinical trials (n=2799 for male and n=2085 for female).

8.9 Race/Ethnicity

No consistent differences in the efficacy and safety of SYMLIN have been observed among patients of differing race/ethnicity in SYMLIN clinical trials (n=4257 for Caucasian, n=229 for black, n=337 for Hispanic or Latino, and n=61 for Asian and one or more races) although the smaller sample sizes for non-Caucasians, particularly Asians, limit conclusions.

10 OVERDOSAGE

Single 10 mg doses of SYMLIN (83 times the maximum recommended dose of 120 mcg for patients with type 2 diabetes) were administered to 3 healthy volunteers. All 3 individuals reported severe nausea associated with vomiting, diarrhea, vasodilatation, and dizziness. No hypoglycemia was reported. Pramlintide has a short half-life (approximately 48 minutes in healthy individuals). Initiate supportive measures in the case of overdose.

11 DESCRIPTION

SYMLIN® (pramlintide acetate) injection is an anti-diabetic medication for use in patients with diabetes treated with insulin. Pramlintide is a synthetic analog of human amylin, a naturally occurring neuroendocrine hormone synthesized by pancreatic beta cells that contributes to glucose control during the postprandial period. Pramlintide is provided as an acetate salt of the synthetic 37-amino acid polypeptide, which differs in amino acid sequence from human amylin by replacement with proline at positions 25 (alanine), 28 (serine), and 29 (serine).

The structural formula of pramlintide acetate is shown below:

Pramlintide acetate is a white powder that has a molecular formula of C171H267N51O53S2• × C2H4O2 (3≤ × ≤8); the molecular weight is 3949.4. Pramlintide acetate is soluble in water.

SYMLIN is formulated as a clear, isotonic, sterile solution for subcutaneous administration. The disposable multidose SymlinPen® pen-injector contains 1000 mcg/mL of pramlintide (as acetate). The formulation contains 2.25 mg/mL of metacresol as a preservative, D-mannitol as a tonicity modifier, acetic acid, sodium acetate as pH modifiers, and water for injection. SYMLIN has a pH of approximately 4.0.

12 CLINICAL PHARMACOLOGY

12.1 Mechanism of Action

Pramlintide is an analog of human amylin. Amylin is colocated with insulin in secretory granules and cosecreted with insulin by pancreatic beta cells in response to food intake. Amylin and insulin show similar fasting and postprandial patterns in healthy individuals (Figure 1).

Figure 1: Secretion Profile of Amylin and Insulin in Healthy Adults

In patients with type 1 and type 2 diabetes, there is reduced secretion from pancreatic beta cells of both insulin and amylin in response to food.

Amylin affects the rate of postprandial glucose appearance through a variety of mechanisms, as determined by nonclinical studies. Amylin slows gastric emptying (i.e., the rate at which food is released from the stomach to the small intestine) without altering the overall absorption of nutrients. In addition, amylin suppresses glucagon secretion (not normalized by insulin alone), which leads to suppression of endogenous glucose output from the liver. Amylin also regulates food intake due to centrally-mediated modulation of appetite.

In human studies, pramlintide, acting as an amylin analog, slows gastric emptying, reduces the postprandial rise in plasma glucagon, and modulates satiety leading to decreased caloric intake.

12.2 Pharmacodynamics

In clinical studies in patients with type 1 diabetes and patients with type 2 diabetes using mealtime insulin, SYMLIN reduced mean postprandial glucose concentrations, reduced glucose fluctuations, and reduced food intake.

Reduction in Postprandial Glucose Concentrations

In a randomized, single-blind, placebo-controlled, crossover study, 19 subjects with type 2 diabetes using insulin lispro, 19 subjects with type 1 diabetes using regular human insulin, and 21 subjects with type 1 diabetes using insulin lispro underwent mixed-meal tests. SYMLIN administered subcutaneously immediately prior to a meal reduced plasma glucose concentrations following the meal when used with mealtime insulin (rapid-acting insulin analogs or regular human insulin) (Figure 2). When rapid-acting insulin analogs were used, plasma glucose concentrations tended to rise during the interval between 150 minutes following SYMLIN injection and the next meal [see Dosage and Administration (2)].

Figure 2: Postprandial Plasma Glucose Profiles in Patients with Type 1 Diabetes or Type 2 Diabetes Receiving SYMLIN and Insulin Compared to Those Receiving Insulin Alone

While SYMLIN reduces postprandial glucose, clinical studies employing a controlled hypoglycemic challenge have demonstrated that SYMLIN does not alter the counter-regulatory hormonal response to insulin-induced hypoglycemia. Likewise, in SYMLIN-treated patients, the perception of hypoglycemic symptoms was not altered with plasma glucose concentrations as low as 45 mg/dL. In a separate clinical trial pramlintide also reduced the 24-hour glucose fluctuations based upon 24-hour glucose monitoring.

Reduced Food Intake

A single, subcutaneous dose of 30 mcg of SYMLIN to patients with type 1 diabetes and 120 mcg of SYMLIN to patients with type 2 diabetes administered 1 hour prior to an unlimited buffet meal was associated with reductions in total caloric intake (placebo-subtracted mean changes of ~21% and 23%, respectively), which occurred without decreases in meal duration.

12.3 Pharmacokinetics

Absorption

The absolute bioavailability of pramlintide following a single subcutaneous dose of SYMLIN is approximately 30% to 40%. Subcutaneous administration of different doses of SYMLIN into the abdominal area or thigh of healthy individuals showed a linear, dose-dependent increase in maximum plasma concentrations (Cmax) and overall exposure (AUC) (Table 5).

Table 5: Mean Pharmacokinetic Parameters Following Administration of Single Subcutaneous Doses of SYMLIN
Subcutaneous Dose (mcg) | AUC (0-∞) (pmol*min/L) | Cmax (pmol/L) | Tmax (min) | Elimination t½ (min)
30 | 3750 | 39 | 21 | 55
60 | 6778 | 79 | 20 | 49
90 | 8507 | 102 | 19 | 51
120 | 11970 | 147 | 21 | 48

Injection of SYMLIN into the arm in obese patients with type 1 or type 2 diabetes showed higher overall exposure (20%-36%) with greater variability (% CV for AUC: 73%-106%), compared with exposure after injection of SYMLIN into the abdominal area or thigh.

Relative bioavailability of pramlintide was not significantly different between obese and non-obese patients and based on BMI or skin fold thickness. Injections administered with 6.0-mm and 12.7-mm needles yielded similar bioavailability.

Distribution

SYMLIN does not extensively bind to red blood cells or albumin (approximately 40% of the drug is unbound in plasma).

Metabolism and Elimination

In healthy individuals, the half-life of pramlintide is approximately 48 minutes. The primary metabolite, Des-lys^1 pramlintide (2-37 pramlintide), is biologically active in vitro. Overall exposure (AUC) to pramlintide is relatively constant with repeat dosing of SYMLIN, indicating no bioaccumulation.

Specific Populations

Renal Impairment

No studies have been conducted in patients with end-stage renal disease. In a single-dose pharmacokinetic study in patients with type 1 diabetes, 60 mcg of SYMLIN was administered to 4 patients with normal renal function (ClCr >90 mL/min), 9 patients with mild renal impairment (ClCr 60-89 mL/min), 5 patients with moderate renal impairment (ClCr 30-59 mL/min) and 3 patients with severe renal impairment (ClCr 15-29 mL/min). No statistically significant differences were noted in total (AUC0-∞) and peak (Cmax) exposure of pramlintide for mild, moderate, and severe renal impairment categories in comparison to patients with normal renal function; although, inter-patient variability in pharmacokinetic parameters was high.

Hepatic Impairment

Pharmacokinetic studies have not been conducted in patients with hepatic impairment.

Geriatric

Pharmacokinetic studies have not been conducted in the geriatric population [see Use in Specific Populations (8.5)].

Pediatric

The efficacy and safety of SYMLIN have not been established in the pediatric population. The use of SYMLIN is not recommended in pediatric patients due to the risk of severe hypoglycemia [see Warnings and Precautions (5.1, 5.2)].

Gender

No study has been conducted to evaluate the effect of gender on pramlintide pharmacokinetics.

Race/Ethnicity

No study has been conducted to evaluate the effect of ethnicity on pramlintide pharmacokinetics.

Drug Interactions

Effect of Pre-Mixing SYMLIN with Insulin

Pharmacokinetic profiles of pramlintide and insulins after coadministration of 30 mcg SYMLIN with different insulins (regular, NPH, and 70/30 premixed formulations of recombinant human insulin) as one subcutaneous injection, premixed in one syringe, were compared to those observed after the coadministration of SYMLIN and different insulins given as separate subcutaneous injections. The effects of premixing on pramlintide pharmacokinetics varied across the different insulin products with a maximum decrease of 40% in pramlintide Cmax and a maximum increase of 36% in pramlintide AUC0-∞. Similarly, effects of premixing on insulin pharmacokinetics varied across different insulin products with a maximum increase of 15% in insulin Cmax and up to a 20% increase in insulin AUC0-600min. Always administer SYMLIN and insulin as separate injections and never mix [see Warnings and Precautions (5.4)].

Acetaminophen

When 1000 mg acetaminophen was given within 0, 1, and 2 hours after a 120 mcg SYMLIN injection in patients with type 2 diabetes (n=24), acetaminophen Cmax decreased by 29%, 23%, and 20%, respectively compared to placebo. The time to maximum plasma concentration or Tmax increased by 72, 48, and 48 minutes, respectively. SYMLIN did not significantly affect acetaminophen Tmax or Cmax when acetaminophen was administered 1 to 2 hours before SYMLIN injection. SYMLIN did not affect acetaminophen AUC regardless of the time of acetaminophen administration in relation to SYMLIN injection.

Oral Contraceptives

When a single dose of a combination oral contraceptive product, containing 30 mcg ethinyl estradiol and 300 mcg norgestrel, was administered 15 minutes after SYMLIN injection (90 mcg dose) in healthy female subjects, there was no statistically significant change in the Cmax and AUC of ethinyl estradiol. However, the norgestrel Cmax was reduced by about 30% and Tmax was delayed by 45 minutes; there was no effect on norgestrel AUC. The clinical relevance of this change is unknown.

Ampicillin

The effect of concomitant administration of SYMLIN and ampicillin was evaluated in healthy volunteers. The administration of a single oral 500 mg dose of ampicillin 15 minutes after a single dose of SYMLIN (90 mcg) did not alter the Cmax or AUC for ampicillin. However, the Tmax for ampicillin was delayed by approximately 60 minutes.

13 NONCLINICAL TOXICOLOGY

13.1 Carcinogenesis, Mutagenesis, Impairment of Fertility

Carcinogenesis

A two-year carcinogenicity study was conducted in CD-1 mice with doses of 0.2, 0.5, and 1.2 mg/kg/day of pramlintide (32, 67, and 159 times the exposure resulting from the human dose of 360 mcg/day based on area under the plasma concentration curve or AUC, respectively). No drug-induced tumors were observed. A two-year carcinogenicity study was conducted in Sprague-Dawley rats with doses of 0.04, 0.2, and 0.5 mg/kg/day of pramlintide (3, 9, and 25 times the exposure resulting from the human dose of 360 mcg/day based on AUC, respectively). No drug-induced tumors were observed in any organ.

Mutagenesis

Pramlintide was not mutagenic in the Ames test and did not increase chromosomal aberration in the human lymphocytes assay. Pramlintide was not clastogenic in the in vivo mouse micronucleus test or in the chromosomal aberration assay utilizing Chinese hamster ovary cells.

Impairment of Fertility

Administration of 0.3, 1, or 3 mg/kg/day of pramlintide (up to 140 times the human dose of 360 mcg/day based on exposure) prior to and during mating had no significant effects on fertility in male or female rats. The highest dose of 3 mg/kg/day resulted in dystocia in 8/12 female rats secondary to maternal toxicity and significant decreases in serum calcium levels.

14 CLINICAL STUDIES

A total of 2333 patients with type 1 diabetes and 1852 patients with type 2 diabetes received SYMLIN in controlled clinical trials.

14.1 Type 1 Diabetes

The efficacy and safety of SYMLIN were evaluated in 3 (26-52-week), randomized, double-blind, placebo-controlled trials in patients with type 1 diabetes. In these studies, insulin adjustments were minimized in order to isolate the SYMLIN effect with insulin adjustments allowed, at the investigator's discretion, when excessive hypoglycemia was encountered. Patients participating in these 3 trials had a mean age of 40 years, a mean duration of diabetes of 17 years, and a mean body mass index of 25.9 kg/m^2.

Table 6 summarizes the 6-month results for those patients assigned to the 30 or 60 mcg dose of SYMLIN or placebo.

Table 6: Mean (SE) Change in HbA1c and Insulin at 6 Months in the Double-Blind, Placebo-Controlled Studies in Patients with Type 1 Diabetes for the Intent-to-Treat Population
 | Trial 1 |  | Trial 2 |  | Trial 3
Variable | SYMLIN (30/60 mcg) | Placebo | SYMLIN (60 mcg) | Placebo | SYMLIN (60 mcg TID) | SYMLIN (60 mcg QID) | Placebo
Variable | N=243 | N=237 | N=148 | N=147 | N=164 | N=161 | N=154
Baseline HbA1c (%) (SD) | 8.7 (1.33) | 8.9 (1.46) | 9.0 (1.12) | 9.1 (1.08) | 8.9 (1.1) | 8.9 (1.0) | 9.0 (1.1)
LSM Change in HbA1c at 6 Months Relative to Baseline (%) (SE) | –0.58 (0.07) [Statistically significant reduction compared to placebo (p-value <0.05).] | –0.25 (0.07) | –0.24 (0.09) | +0.08 (0.09) | –0.44 (0.07) | –0.44 (–0.07) | –0.19 (0.08)
Placebo- Subtracted LSM change in HbA1c at 6 Months (%) | –0.34 | NA | –0.32 | NA | –0.25 | –0.25 | NA
Mean Insulin Doses at Baseline: Mealtime/Bolus (U) (SE) | NM | NM | 29.5 (1.4) | 28.5 (1.1) | 19.9 (1.2) | 19.8 (2.2) | 19.8 (1.3)
Mean Change in Insulin Doses (U) at 6 Months: Mealtime/Bolus (SE) | NM | NM | –2.0 (0.5) | +0.3 (0.4) | +0.6 (0.8) | –0.8 (0.7) | +0.3 (1.4)
Mean Insulin Doses at Baseline: Basal (U) (SE) | NM | NM | 21.0 (1.1) | 21.0 (1.1) | 33.1 (1.7) | 33.7 (1.6) | 31.9 (1.8)
Mean Change in Insulin Doses (U) at 6 Months: Basal (SE) | NM | NM | +0.2 (0.3) | –0.3 (0.4) | –0.1; (0.9) | –0.6 (0.7) | +0.6 (0.7)
SD: standard deviation; LSM: least squares mean; SE: standard error; U: Units; NM: not measured; TID: 3 times a day; QID: 4 times a day.

In the three studies, from a mean baseline body weight of 75.3 kg, 73.3 kg, and 76.6 kg, respectively, after randomization there were corresponding mean reductions of –0.8 kg, –1.6 kg, and –1.3 kg (60 mcg TID) and –0.8 kg (60 mcg QID) in the SYMLIN treatment group compared to mean increases of +0.8 kg, +0.4 kg, and +0.7 kg in the placebo treatment group.

SYMLIN Dose-Titration Study

A dose-titration study of SYMLIN was conducted in patients with type 1 diabetes who had a mean age of 41 years, a mean duration of diabetes of 20 years, and a mean body mass index of 28 kg/m^2. Patients with a mean baseline HbA1c of 8.1% (range 6.5%-10.7%) were randomized to receive either SYMLIN or placebo, both administered before major meals as add-on to insulin therapy. SYMLIN was initiated at a dose of 15 mcg and titrated upward at weekly intervals in 15 mcg increments to maintenance doses of 30 or 60 mcg, based on whether patients experienced nausea. Upon initiation of SYMLIN, the insulin dose (mostly the mealtime insulin) was reduced by 30% to 50% in order to minimize the occurrence of hypoglycemia. Once the maintenance dose of SYMLIN was reached, insulin dose adjustments were made according to standard clinical practice, based on pre- and post-meal blood glucose monitoring.

Table 7 summarizes the 6-month results for the dose-titration study.

Table 7: Mean (SE) Change in HbA1c and Insulin at 6 Months in the Dose-Titration Study in Patients with Type 1 Diabetes for Intent-to-Treat Population
Variable | SYMLIN (all doses) | Placebo
 | N=148 | N=147
Mean Baseline HbA1c (%), (SD) | 8.1 (0.8) | 8.1 (0.8)
LSM Change in HbA1c at Week 29 Relative to Baseline (%) | –0.47 (0.07) | –0.49 (0.07)
Placebo-Subtracted LSM change in HbA1c at 6 Months (%) (SE) | 0.03 (0.10) | NA
Mean Insulin Doses at Baseline: Mealtime/Bolus (U) (SD) | 26.5 (14.2) | 28.4 (16.3)
Mean Percent Change in Insulin Doses (U) at 6 Months: Mealtime/Bolus (SE) | –7.1 (0.9) [Statistically significant reduction compared to placebo (p-value <0.05).] | –2.4 (1.2)
Mean Insulin Doses at Baseline: Basal (U) (SD) | 29.4 (19.6) | 28.1 (17.5)
Mean Change in Insulin Doses (U) at 6 Months: Basal (SE) | +1.4 (0.9) | +2.6 (1.2)
SD: standard deviation; LSM: least squares mean; SE: standard error; U: Units.

In the dose titration study, from mean baseline body weight of 81.5 kg, after randomization there was a mean reduction of –1.33 kg in the SYMLIN treatment group compared to a mean increase of +1.25 kg in the placebo treatment group.

14.2 Type 2 Diabetes

The efficacy and safety of SYMLIN were evaluated in 2 (a 26-week and a 52-week) randomized, double-blind, placebo-controlled trials in patients with type 2 diabetes. These trials enrolled patients with inadequate glycemic control (HbA1c >8%) on fixed dose insulin. In both trials, SYMLIN or placebo was added to existing insulin therapies. Concomitant use of a sulfonylurea and/or metformin was permitted. Insulin doses were to be kept as stable as possible throughout the treatment period to isolate the SYMLIN effect.

Patients participating in these 2 trials had a mean age of 57 years and a mean duration of diabetes of 13 years. Mean body mass index was 32.9 kg/m^2 for SYMLIN and 32.2 kg/m^2 for placebo.

Table 8 summarizes the 6-month results for each trial for those patients assigned to the 120 mcg dose of SYMLIN and placebo.

Table 8: Mean (SE) Change in HbA1c and Insulin at 6 Months in the Double-Blind, Placebo-Controlled Studies in Patients with Type 2 Diabetes for the Intent-to-Treat Population
 | Trial 1 |  | Trial 2
Variable | SYMLIN (120 mcg) | Placebo | SYMLIN (120 mcg) | Placebo
 | N=166 | N=161 | N=126 | N=123
Baseline HbA1c (%) (SD) | 9.0 (0.08) | 9.3 (0.10) | 9.3 (1.1) | 9.5 (1.4)
LSM Change in HbA1c at 6 Months Relative to Baseline (%) (SE) | –0.66 (0.08) [dStatistically significant reduction compared to placebo (p-value <0.05).] | –0.32 (0.09) | –0.36 (0.10) | –0.06 (0.10)
Placebo-Subtracted LSM change in HbA1c at 6 Months (%) | –0.34 | NA | –0.30 | NA
Insulin Dose at Baseline: Mealtime/Bolus (U) (SE) | 20.7 (1.6) | 21.4 (1.5) | 22.2 (1.8) | 22.0 (1.6)
Mean Change in Insulin Doses (U) at 6 Months: Mealtime/Bolus (SE) | –0.7 (0.5) | –0.3 (0.6) | –0.0 (0.8) | +1.6 (0.7)
Insulin Dose at Baseline: Basal (U) (SE) | 48.0 (1.9) | 52.4 (2.1) | 33.2 (1.4) | 30.9 (1.6)
Mean Change in Insulin Doses (U) at 6 Months: Basal (SE) | +0.01 (0.8) | +1.1 (1.0) | –1.2 (0.8) | +1.3 (0.7)
SD: standard deviation; LSM: least squares mean; SE: standard error; U: Units.

In both studies, from a mean baseline body weight of 96.7 kg, and 85.6 kg, respectively, after randomization there were corresponding mean reductions of –1.4 kg, and –1.6 kg in the SYMLIN treatment group compared to mean increases of +0.3 kg, and +0.1 kg in the placebo treatment group.

16 HOW SUPPLIED/STORAGE AND HANDLING

SYMLIN Injection is available in the following package sizes:

- SymlinPen® 60 pen-injector, containing 1000 mcg/mL pramlintide (as acetate)
  Two 1.5 mL disposable multidose pen-injectors
  (NDC 0310-6615-02)
- SymlinPen® 120 pen-injector, containing 1000 mcg/mL pramlintide (as acetate)
  Two 2.7 mL disposable multidose pen-injectors
  (NDC 0310-6627-02)

Storage and Handling

SYMLIN pen-injectors not in use: Refrigerate (2°C to 8°C; 36°F to 46°F), and protect from light. Do not freeze. Do not use if product has been frozen. Unused SYMLIN (opened or unopened) should not be used after the expiration (EXP) date printed on the carton and the label.

SYMLIN pen-injectors in use: After first use, refrigerate or keep at a temperature not greater than 86°F (30°C) for 30 days. Use within 30 days, whether or not refrigerated.

Storage conditions are summarized in Table 9.

Table 9: Storage Conditions
Dosage Form | Unopened (not in use) Refrigerated | Open (in use) Refrigerated or Temperature up to 86°F (30°C)
1.5 mL pen-injector | Until Expiration Date | Use Within 30 Days
2.7 mL pen-injector

17 PATIENT COUNSELING INFORMATION

Advise the patient to read the FDA-approved patient labeling (Medication Guide).

Risk of Hypoglycemia

Discuss the risk and consequences of hypoglycemia and approaches to minimize its occurrence. Inform patients about the importance of self-management practices including glucose monitoring and timing of dosing. In addition, reinforce the importance of adherence to meal planning, physical activity, recognition and management of hypoglycemia and hyperglycemia, and assessment of diabetes complications.

Never Share a SymlinPen Between Patients

Advise patients that they must never share a SymlinPen with another person, even if the needle is changed, because doing so carries a risk for transmission of blood-borne pathogens.

Never Mix SYMLIN and Insulin

Inform patients that SYMLIN and insulin should always be administered as separate injections and never be mixed.

Show patients how to administer SYMLIN using the pen-injector. Advise patients to use a new needle for each injection.

Instructions

Instruct patients on the proper injection technique and proper storage of SYMLIN. Refer patients to the SYMLIN Medication Guide and Patient Instructions for Use for additional information.

Distributed by:

AstraZeneca Pharmaceuticals LP
Wilmington, DE 19850

SYMLIN and SymlinPen are registered trademarks of the AstraZeneca group of companies.

MEDICATION GUIDE

SYMLIN® (SĬM-lĭn)
(pramlintide acetate)

injection for subcutaneous use

Read this Medication Guide and Instructions for Use that come with your SYMLIN before you start using it and each time you get a refill. There may be new information. This Medication Guide does not take the place of talking to your healthcare provider about your medical condition or treatment.

What is the most important information I should know about SYMLIN?

SYMLIN can cause serious side effects, including:

- severe low blood sugar (hypoglycemia). Even when SYMLIN is carefully added to your mealtime insulin therapy, your blood sugar may drop too low, especially if you have type 1 diabetes. If this severe low blood sugar (hypoglycemia) happens, it is seen within 3 hours after a SYMLIN injection. Symptoms of severe low blood sugar and low blood sugar include:
  - lightheadedness
  - dizziness
  - shakiness
  - sweating
  - hunger
  - fast heartbeat
  - trouble concentrating or confusion
  - change in vision
  - headache
  - irritability
  - drowsiness

People who have severely low blood sugar have had injuries while driving their car, operating heavy machinery or doing other dangerous activities. You and your healthcare provider should talk about a plan to treat low blood sugar. You should have fast-acting sugar (such as hard candy, glucose tablets, juice) or glucagon for injection with you at all times. Call your healthcare provider if you have severe low blood sugar or if you have low blood sugar more often than normal.

You have a higher chance of getting severe low blood sugar if you:
  1. do not follow your healthcare provider’s instructions to reduce your insulin use before meals
  2. use more SYMLIN or insulin than prescribed by your healthcare provider
  3. change your insulin dose without checking your blood sugar
  4. eat less food than your usual meal
  5. are sick and cannot eat
  6. are more active than usual
  7. have a low blood sugar level before eating
  8. drink alcohol
SYMLIN is used with insulin to lower blood sugar, especially high blood sugar that happens after meals.
SYMLIN is taken at mealtimes. The use of SYMLIN does not replace your daily insulin but may lower the amount of insulin you need, especially before meals.

Do not share your SymlinPen with other people, even if the needle has been changed. You may give other people a serious infection, or get a serious infection from them.

What is SYMLIN?

SYMLIN is an injectable prescription medicine used to treat adults with type 1 and type 2 diabetes to control blood sugar. SYMLIN is used when your mealtime insulin dose has not controlled your blood sugar well enough.

It is not known if SYMLIN is safe and effective in children.

Who should not use SYMLIN?

Do not use SYMLIN if you:

- are allergic to SYMLIN or any ingredients in SYMLIN. See the end of this Medication Guide for a complete list of ingredients in SYMLIN.
- cannot tell when your blood sugar is low (hypoglycemia unawareness)
- have a stomach problem called gastroparesis. This is when your stomach does not empty as fast as it should.

What should I tell my healthcare provider before using SYMLIN?

Before you use SYMLIN, tell your healthcare provider about all of your medical conditions, including if you:

- are pregnant or plan to become pregnant. It is not known if SYMLIN will harm your unborn baby. You and your healthcare provider should decide how to best control your blood sugar levels during pregnancy.
- are breastfeeding or plan to breastfeed. It is not known if SYMLIN passes into your breast milk. You and your healthcare provider should decide about the best way to feed your baby if you are using SYMLIN.

Tell your healthcare provider about all the medicines you take, including prescription and over-the-counter medicines, vitamins, and herbal supplements. SYMLIN slows stomach emptying and can affect medicines that need to pass through the stomach quickly.

How should I use SYMLIN?

- Read the “Instructions for Use” and the Medication Guide and that come with your SYMLIN for information about the right way to use SYMLIN.
- Use SYMLIN exactly as your healthcare provider tells you to use it.
- Your healthcare provider will tell you how much SYMLIN to use and when to use it.
- Your healthcare provider may change your dose if needed.
- If you stop taking SYMLIN for any reason, such as surgery or illness, talk to your healthcare provider about how to re-start SYMLIN.
- To reduce the risk of hypoglycemia, it is important that you plan your meals and physical activity every day while you use SYMLIN. Plan for what you will eat and when you will eat your meals.
- The amount of SYMLIN you use will depend on whether you have type 1 or type 2 diabetes.
- The way you inject SYMLIN is similar to the way you inject insulin. Inject SYMLIN under the skin of your stomach area (abdomen) or upper leg (thigh). Inject SYMLIN at a site that is more than 2 inches away from your insulin injection. Do not inject SYMLIN and insulin in the same site.
- To help reduce the chances of getting a reaction at the injection site, allow SYMLIN to come to room temperature before injecting.
- Use a new needle for each SYMLIN injection. Do not reuse or share your needles with other people. You may give other people a serious infection, or get a serious infection from them.
- Never mix SYMLIN and insulin. Insulin can affect SYMLIN when they are mixed together.
- Do not use SYMLIN if the liquid looks cloudy.
- If you take more than your prescribed dose of SYMLIN, you may get nauseous or vomit, and may not be able to eat the amount of food you usually eat. If you take more SYMLIN than your prescribed dose, pay careful attention to the amount of insulin you use because you may be at more risk for low blood sugar. Contact your healthcare provider for guidance.
- If you miss or forget a dose of SYMLIN, wait until the next meal and take your usual dose of SYMLIN at that meal. Do not take more than your usual dose of SYMLIN.
- Do not share your SymlinPen with other people, even if the needle is changed. You may give other people a serious infection or get a serious infection from them.

Using SYMLIN and insulin with type 1 diabetes:

- When starting SYMLIN, you will need to reduce your dose of mealtime insulin. Your healthcare provider will tell you how to reduce your dose of mealtime insulin the right way.
- You must check your blood sugar as often as your healthcare provider tells you to, which may include before and after every meal and at bedtime.
- The usual starting dose of SYMLIN for people who have type 1 diabetes is 15 micrograms (mcg) injected under your skin.
- Inject SYMLIN under your skin (subcutaneously) just before a major meal. A major meal must have at least 250 calories or 30 grams of carbohydrate.
- If you have not had any nausea for 3 days or more after your dose of SYMLIN is changed, your healthcare provider may tell you to slowly increase your dose of SYMLIN. Do not increase your dose of SYMLIN unless your healthcare provider tells you to.
- Tell your healthcare provider right away if you have nausea or low blood sugar after your dose of SYMLIN is changed. Your healthcare provider will tell you what to do.
- Your healthcare provider may make changes to your insulin dose to better control your blood sugar. Your healthcare provider should tell you what the right dose of insulin is for you.

Using SYMLIN and insulin with type 2 diabetes:

- When starting SYMLIN, you will need to reduce your dose of mealtime insulin. Your healthcare provider will tell you how to reduce your dose of mealtime insulin the right way.
- You must check your blood sugar as often as your healthcare provider advises you to, which may include before and after every meal and at bedtime.
- The usual starting dose of SYMLIN for people who have type 2 diabetes is 60 micrograms (mcg) injected under your skin.
- Inject SYMLIN under your skin (subcutaneously) just before a major meal. A major meal must have at least 250 calories or 30 grams of carbohydrate.
- If you have not had any nausea for 3 days or more after your dose of SYMLIN is changed, your healthcare provider may tell you to increase your dose of SYMLIN. Do not increase your dose of SYMLIN unless your healthcare provider tells you to.
- Tell your healthcare provider right away if you have nausea or low blood sugar after your dose of SYMLIN is changed. Your healthcare provider will tell you what to do.
- Your healthcare provider may make changes to your insulin dose to better control your blood sugar. Your healthcare provider should tell you what the right dose of insulin is for you.

What should I avoid while taking SYMLIN?

- See “What is the most important information I should know about SYMLIN?”
- Do not drive, operate machinery, or do other dangerous activities until you know how SYMLIN affects you. Talk to your healthcare provider about the activities you should avoid.
- Alcohol. Drinking alcohol may increase your chances of getting severe low blood sugar.

What are the possible side effects of SYMLIN?

SYMLIN may cause serious side effects, including:

- See “What is the most important information I should know about SYMLIN?”
- injection site reactions. SYMLIN may cause bruising, swelling, or itching at the injection site.

The most common side effects of SYMLIN include:

- nausea
- vomiting
- decreased appetite
- stomach pain
- headache

Tell your healthcare provider if you have any side effect that bothers you or that does not go away.

These are not all the possible side effects of SYMLIN. For more information, ask your healthcare provider or pharmacist.

Call your doctor for medical advice about side effects. You may report side effects to FDA at 1-800-FDA-1088.

How should I store SYMLIN?

Unopened SYMLIN:

- Keep SYMLIN in the refrigerator between 36°F to 46°F (2°C to 8°C), until you are ready to use it.
- Do not freeze. Do not use SYMLIN if it has been frozen.
- Keep unopened SYMLIN out of the light.

Opened SYMLIN:

- Keep SYMLIN either in the refrigerator or at room temperature between 36°F to 86°F (2°C to 30°C) for up to 30 days.
- Throw away used SYMLIN after 30 days of use, even if the pen still has medicine in it.
- Do not use SYMLIN (opened or unopened) after the expiration (EXP) date printed on the carton and the label.

Keep SYMLIN and all medicines out of the reach of children.

General information about the safe and effective use of SYMLIN:

Medicines are sometimes prescribed for purposes other than those listed in a Medication Guide. Do not use SYMLIN for a condition for which it was not prescribed. Do not give SYMLIN to other people, even if they have the same symptoms that you have. It may harm them.

This Medication Guide summarizes the most important information about SYMLIN. If you would like more information, talk with your healthcare provider. You can ask your pharmacist or healthcare provider for information about SYMLIN that is written for health professionals.

More information, go to www.SYMLIN.com or call 1-800-236-9933.

What are the ingredients in SYMLIN?

Active ingredient: pramlintide acetate

Inactive ingredients: metacresol, D-mannitol, acetic acid, and sodium acetate

This Medication Guide has been approved by the U.S. Food and Drug Administration.

SYMLIN and SymlinPen are registered trademarks of the AstraZeneca group of companies.

Distributed by:

AstraZeneca Pharmaceuticals LP

Wilmington, DE 19850

Revised: February 2015

Instructions for Use

SymlinPen® (SĬM-lĭnPεn) 120

(pramlintide acetate)
Pen-Injector

Read the Medication Guide and these Instructions for Use before you start using SYMLIN and each time you get a refill. There may be new information.

Do not share your SymlinPen with other people, even if the needle has been changed. You may give other people a serious infection, or get a serious infection from them.

Important:

- Ask your healthcare provider about your dose of SYMLIN and how to inject SYMLIN the right way before you inject it for the first time.
- Use a new needle for each SYMLIN injection. Do not reuse or share your needles with other people. You may give other people a serious infection, or get a serious infection from them.
- This SymlinPen is not recommended for use by the blind or visually impaired without the assistance of a person trained in the proper use of this SymlinPen.
- Check SYMLIN before you use it. SYMLIN should be clear and colorless. Do not use SYMLIN if the liquid looks cloudy or colored or has lumps or particles in it.
- Your SymlinPen may look empty because SYMLIN is a clear and colorless liquid.
- Small bubbles will not hurt you or affect your dose of SYMLIN.
- Do not transfer SYMLIN from your SymlinPen into a syringe.
- Do not inject your dose of SYMLIN if you:
  ∘ have low blood sugar (hypoglycemia)
  ∘ do not plan to eat. Do not inject SYMLIN if you skip a meal. Wait until the next meal and take your usual dose of SYMLIN at that meal.
  ∘ plan to eat a meal with less than 250 calories or 30 grams of carbohydrate
  ∘ are sick and cannot eat your usual meal
  ∘ are having surgery or a medical test where you cannot eat
- If you take more than your prescribed dose of SYMLIN, you may get nauseous or vomit, and may not be able to eat the amount of food you usually eat. If you take more SYMLIN than your prescribed dose, pay careful attention to the amount of insulin you use because you may be at more risk for low blood sugar. Contact your healthcare provider for guidance.

Supplies you will need to give each injection of SYMLIN:

- SymlinPen® 120 Pen-Injector (Pen) (See Figure A)
- a new SymlinPen compatible needle (See Figure B). Pen needles are not included. Use 29, 30, or 31 gauge disposable pen needles. Ask your healthcare provider which needle gauge and length is best for you.
- alcohol swab
- 1 sharps container for throwing away used SymlinPens and needles. See “Disposing of used SymlinPens and needles” at the end of these Instructions for Use.

(Figure A)

(Figure B)

Preparing your SymlinPen:

- Wash your hands with soap and water.
- Check the SymlinPen label before each use to make sure you have the right SymlinPen.
- Check the expiration date (EXP) on the SymlinPen label (See Figure A). Do not use the SymlinPen past the expiration date printed on the label.
- Check the liquid in your SymlinPen to make sure you have enough SYMLIN left in your SymlinPen to load your correct dose.
  ∘ The lines on the cartridge show about how much SYMLIN is left in your SymlinPen. When the top of the plunger is at the thickest line on the cartridge, your SymlinPen is almost empty (See Figure C).

(Figure C)

Attaching a Needle:

Step 1:

- Pull the pen cap straight off the SymlinPen and wipe the rubber seal with an alcohol swab.

Figure D

Step 2:

- Get a new needle.
- Peel off the paper tab and throw it away.

Figure E

Step 3:

- Push the capped needle straight onto the end of the SymlinPen and twist the needle clockwise until it is tight.

Figure F

Step 4:

- Pull off the outer needle cover. Do not throw it away.
- Pull off the inner needle cover and throw it away.

Figure G

New Pen Setup - Priming your SymlinPen:

Note:

- Steps 5 through 7 are only required if you are using your SymlinPen for the first time. Do not repeat Step 1 through 4 before each dose.
  ∘ If you have already primed your SymlinPen, go to Step 8 for instructions about giving your scheduled dose.

Step 5:
2. Turn the dial to select 60 mcg.
  ∘ You should see the number 60 in the window.

Figure H

Step 6:
2. Pull the knob straight out as far as it will go. You should hear a “clicking” sound while you are pulling the knob out.

Figure I

Step 7:
2. Hold your SymlinPen with the needle pointing up. Push the knob all the way in until it stops. You should hear a “clicking” sound while you are pushing the knob in.
  ∘ A stream of liquid should be seen from the needle.
    - If you do not see a stream of liquid, repeat Step 6 and Step 7 (you may repeat up to 3 times).
    - If you still do not see a stream of liquid after 3 attempts, change the needle and repeat Step 6 and Step 7. If you still do not see a stream of liquid, call Information Support.

Figure J

Selecting your routine dose:

Step 8:

- Turn the dial to select the correct dose you need to inject.

Figure K

Step 9:

- Pull the knob straight out as far as it will go. You should hear a “clicking” sound while you are pulling the knob out.

Figure L

Step 10:

- Turn the knob forward or backward until you see the correct dose you need to inject.
- Check that you see the line to make sure you have loaded your full dose. You should see a line, arrow, and the number of your dose.
  ∘ If you do not see a line, arrow, and the number of your dose, do not inject the dose. Point the needle away from you, push the knob all the way in until it stops, then repeat Step 8 to Step 10.
  ∘ Once the knob has been pulled out, the dial will not move and you cannot reset your dose. If correct dose was not selected, push in the knob to discard the dose and repeat the instructions. If the knob is pushed in all the way, and you cannot turn the dial, call Information Support.

Figure M

Figure N

Giving your SYMLIN injection:

- Inject your SYMLIN exactly as your doctor has shown you.
- Change (rotate) injection sites for SYMLIN. Inject SYMLIN at a site that is more than 2 inches away from your insulin injection. Do not inject SYMLIN and insulin in the same site.
- To help reduce the chances of getting a reaction at the injection site, let SYMLIN come to room temperature before you inject it.

Step 11:
2. Choose your injection site.
3. SYMLIN is injected under the skin (subcutaneously) of your stomach area (abdomen) or upper leg (thigh).
4. Wipe the skin with an alcohol swab, and let the injection site dry before you inject your dose.

Figure O

Step 12:
2. Insert the needle into your skin.

Figure P

Step 13:
2. Put your thumb on the knob and push the knob all the way in until it stops. You should hear the “clicking” as you push and hold the knob in and slowly count to 10 to give your full dose.

Figure Q

Step 14:

- Pull the needle out of your skin.
- If you see blood after you take the needle out of your skin, press the injection site lightly with a piece of gauze or an alcohol swab. Do not rub the area.
  ∘ A drop or 2 of liquid on the needle tip is normal. It will not affect your dose.
  ∘ If you see more than 2 drops, you may not have received your full dose. Do not inject another dose. Talk to your doctor for help.

Figure R

Step 15:

- Carefully replace the outer needle cover by pushing straight onto the end of the SymlinPen.

Figure S

Step 16:

- Unscrew the capped needle counterclockwise with the outer needle cover on it and throw it away.
- Do not store the SymlinPen with the needle attached or with the knob pulled out to prevent air bubbles.

Figure T

Step 17:

- Replace the pen cap.

Figure U

After your injection:

- Put your used needles and SymlinPen in an FDA-cleared sharps disposal container right away after use. Do not throw away (dispose of) loose needles and syringes in your household trash.
  ∘ If you do not have an FDA-cleared sharps disposal container, you may use a household container that is:
    - made of a heavy-duty plastic,
    - can be closed with a tight-fitting, puncture-resistant lid, without sharps being able to come out,
    - upright and stable during use,
    - leak-resistant, and
    - properly labeled to warn of hazardous waste inside the container.
  ∘ When your sharps disposal container is almost full, you will need to follow your community guidelines for the right way to dispose of your sharps disposal container. There may be state or local laws about how you should throw away used needles and SymlinPen. For more information about safe sharps disposal, and for specific information about sharps disposal in the state that you live in, go to the FDA’s website at: http://www.fda.gov/safesharpsdisposal
  ∘ Do not dispose of your used sharps disposal container in your household trash unless your community guidelines permit this. Do not recycle your used sharps disposal container.

How should I store my SymlinPen?

Unused SymlinPens:

- Keep SYMLIN in the refrigerator between 36°F to 46°F (2°C to 8°C), until you are ready to use it.
- Do not freeze. Do not use SYMLIN if it has been frozen.
- Keep unopened SYMLIN out of the light.

Used SymlinPens:

- Store SymlinPens in the refrigerator or at room temperature between 36°F to 86°F (2°C to 30°C) for up to 30 days.
- Throw away used SymlinPens after 30 days of use, even if a used SymlinPen still has medicine in it.
- Do not use SymlinPens (opened or unopened) after the expiration (EXP) date printed on the carton and the label.

General information about the safe and effective use of SymlinPens.

- If you drop your SymlinPen, you should prime it before you use it to make sure your SymlinPen works.
- Do not use your SymlinPen if any part looks broken or damaged.
- Keep SYMLIN and all medicines out of the reach of children.
- It is not known if SYMLIN is safe and effective in children.

If you are having problems using your SymlinPen, go to www.SYMLIN.com or call Information Support at 1-800-236-9933.

These Instructions for Use have been approved by the U.S. Food and Drug Administration.

SYMLIN and SymlinPen are registered trademarks of the AstraZeneca group of companies.

Distributed by:

AstraZeneca Pharmaceuticals LP

Wilmington, DE 19850

Revised: March 2015

Instructions for Use

SymlinPen® (SĬM-lĭnPεn) 60

(pramlintide acetate)
Pen-Injector

Read the Medication Guide and these Instructions for Use before you start using SYMLIN and each time you get a refill. There may be new information.

Do not share your SymlinPen with other people, even if the needle has been changed. You may give other people a serious infection, or get a serious infection from them.

Important:

- Ask your healthcare provider about your dose of SYMLIN and how to inject SYMLIN the right way before you inject it for the first time.
- Use a new needle for each SYMLIN injection. Do not reuse or share your needles with other people. You may give other people a serious infection, or get a serious infection from them.
- This SymlinPen is not recommended for use by the blind or visually impaired without the assistance of a person trained in the proper use of this SymlinPen.
- Check SYMLIN before you use it. SYMLIN should be clear and colorless. Do not use SYMLIN if the liquid looks cloudy or colored or has lumps or particles in it.
- Your SymlinPen may look empty because SYMLIN is a clear and colorless liquid.
- Small bubbles will not hurt you or affect your dose of SYMLIN.
- Do not transfer SYMLIN from your SymlinPen into a syringe.
- Do not inject your dose of SYMLIN if you:
  ∘ have low blood sugar (hypoglycemia)
  ∘ do not plan to eat. Do not inject SYMLIN if you skip a meal. Wait until the next meal and take your usual dose of SYMLIN at that meal.
  ∘ plan to eat a meal with less than 250 calories or 30 grams of carbohydrate
  ∘ are sick and cannot eat your usual meal
  ∘ are having surgery or a medical test where you cannot eat
- If you take more than your prescribed dose of SYMLIN, you may get nauseous or vomit, and may not be able to eat the amount of food you usually eat. If you take more SYMLIN than your prescribed dose, pay careful attention to the amount of insulin you use because you may be at more risk for low blood sugar. Contact your healthcare provider for guidance.

Supplies you will need to give each injection of SYMLIN:

- SymlinPen® 60 Pen-Injector (Pen) (See Figure A)
- a new SymlinPen compatible needle (See Figure B). Pen needles are not included. Use 29, 30, or 31 gauge disposable pen needles. Ask your healthcare provider which needle gauge and length is best for you.
- alcohol swab
- 1 sharps container for throwing away used SymlinPens and needles. See “Disposing of used SymlinPens and needles” at the end of these Instructions for Use.

(Figure A)

(Figure B)

Preparing your SymlinPen:

- Wash your hands with soap and water.
- Check the SymlinPen label before each use to make sure you have the right SymlinPen.
- Check the expiration date (EXP) on the SymlinPen label (See Figure A). Do not use the SymlinPen past the expiration date printed on the label.
- Check the liquid in your SymlinPen to make sure you have enough SYMLIN left in your SymlinPen to load your correct dose.
  ∘ The lines on the cartridge show about how much SYMLIN is left in your SymlinPen. When the top of the plunger is at the thickest line on the cartridge, your SymlinPen is almost empty (See Figure C).

(Figure C)

Attaching a Needle:

Step 1:

- Pull the pen cap straight off the SymlinPen and wipe the rubber seal with an alcohol swab.

Figure D

Step 2:

- Get a new needle
- Peel off the paper tab and throw it away.

Figure E

Step 3:

- Push the capped needle straight onto the end of the SymlinPen and twist the needle clockwise until it is tight.

Figure F

Step 4:

- Pull off the outer needle cover. Do not throw it away.
- Pull off the inner needle cover and throw it away.

Figure G

New Pen Setup - Priming your SymlinPen:

Note:

- Steps 5 through 7 are only required if you are using your SymlinPen for the first time. Do not repeat Step 1 through 4 before each dose.
- If you have already primed your SymlinPen, go to Step 8 for instructions about giving your scheduled dose.

Step 5:

- Turn the dial to select 15 mcg.
  ∘ You should see the number 15 in the window.

Figure H

Step 6:

- Pull the knob straight out as far as it will go. You should hear a “clicking” sound while you are pulling the knob out.

Figure I

Step 7:

- Hold your SymlinPen with the needle pointing up. Push the knob all the way in until it stops. You should hear a “clicking” sound while you are pushing the knob in.
  ∘ A stream of liquid should be seen from the needle.
    - If you do not see a stream of liquid, repeat Step 6 and Step 7 (you may repeat up to 6 times).
    - If you still do not see a stream of liquid after 6 attempts, change the needle and repeat Step 6 and Step 7. If you still do not see a stream of liquid, call Information Support.

Figure J

Selecting your routine dose:

Step 8:

- Turn the dial to select the correct dose you need to inject.

Figure K

Step 9:

- Pull the knob straight out as far as it will go. You should hear a “clicking” sound while you are pulling the knob out.

Figure L

Step 10:

- Turn the knob forward or backward until you see the correct dose you need to inject.
- Check that you see the line to make sure you have loaded your full dose. You should see a line, arrow, and the number of your dose.
  ∘ If you do not see a line, arrow, and the number of your dose, do not inject the dose. Point the needle away from you, push the knob all the way in until it stops, then repeat Step 8 to Step 10.
  ∘ Once the knob has been pulled out, the dial will not move and you cannot reset your dose. If correct dose was not selected, push in the knob to discard the dose and repeat the instructions. If the knob is pushed in all the way, and you cannot turn the dial, call Information Support.

Figure M

Figure N

Giving your SYMLIN injection:

- Inject your SYMLIN exactly as your doctor has shown you.
- Change (rotate) injection sites for SYMLIN. Inject SYMLIN at a site that is more than 2 inches away from your insulin injection. Do not inject SYMLIN and insulin in the same site.
- To help reduce the chances of getting a reaction at the injection site, let SYMLIN come to room temperature before you inject it.

Step 11:

- Choose your injection site.
- SYMLIN is injected under the skin (subcutaneously) of your stomach area (abdomen) or upper leg (thigh).
- Wipe the skin with an alcohol swab, and let the injection site dry before you inject your dose.

Figure O

Step 12:

- Insert the needle into your skin.

Figure P

Step 13:

- Put your thumb on the knob and push the knob all the way in until it stops. You should hear the “clicking” as you push and hold the knob in and slowly count to 10 to give your full dose.

Figure Q

Step 14:

- Pull the needle out of your skin.
- If you see blood after you take the needle out of your skin, press the injection site lightly with a piece of gauze or an alcohol swab. Do not rub the area.
  ∘ A drop or 2 of liquid on the needle tip is normal. It will not affect your dose.
  ∘ If you see more than 2 drops, you may not have received your full dose. Do not inject another dose. Talk to your doctor for help.

Figure R

Step 15:

- Carefully replace the outer needle cover by pushing straight onto the end of the SymlinPen.

Figure S

Step 16:

- Unscrew the capped needle counterclockwise with the outer needle cover on it and throw it away.
- Do not store the SymlinPen with the needle attached or with the knob pulled out to prevent air bubbles.

Figure T

Step 17:

- Replace the pen cap.

Figure U

After your injection:

- Put your used needles and SymlinPen in an FDA-cleared sharps disposal container right away after use. Do not throw away (dispose of) loose needles and syringes in your household trash.
  ∘ If you do not have an FDA-cleared sharps disposal container, you may use a household container that is:
    - made of a heavy-duty plastic,
    - can be closed with a tight-fitting, puncture-resistant lid, without sharps being able to come out,
    - upright and stable during use,
    - leak-resistant, and
    - properly labeled to warn of hazardous waste inside the container.
  ∘ When your sharps disposal container is almost full, you will need to follow your community guidelines for the right way to dispose of your sharps disposal container. There may be state or local laws about how you should throw away used needles and SymlinPen. For more information about safe sharps disposal, and for specific information about sharps disposal in the state that you live in, go to the FDA’s website at: http://www.fda.gov/safesharpsdisposal
  ∘ Do not dispose of your used sharps disposal container in your household trash unless your community guidelines permit this. Do not recycle your used sharps disposal container.

How should I store my SymlinPen?

Unused SymlinPens:

- Keep SYMLIN in the refrigerator between 36°F to 46°F (2°C to 8°C), until you are ready to use it.
- Do not freeze. Do not use SYMLIN if it has been frozen.
- Keep unopened SYMLIN out of the light.

Used SymlinPens:

- Store SymlinPens in the refrigerator or at room temperature between 36°F to 86°F (2°C to 30°C) for up to 30 days.
- Throw away used SymlinPens after 30 days of use, even if a used SymlinPen still has medicine in it.
- Do not use SymlinPens (opened or unopened) after the expiration (EXP) date printed on the carton and the label.

General information about the safe and effective use of SymlinPens.

- If you drop your SymlinPen, you should prime it before you use it to make sure your SymlinPen works.
- Do not use your SymlinPen if any part looks broken or damaged.
- Keep SYMLIN and all medicines out of the reach of children.
- It is not known if SYMLIN is safe and effective in children.
If you are having problems using your SymlinPen, go to www.SYMLIN.com or call Information Support at 1-800-236-9933.

These Instructions for Use have been approved by the U.S. Food and Drug Administration.

SYMLIN and SymlinPen are registered trademarks of the AstraZeneca group of companies.

Distributed by:

AstraZeneca Pharmaceuticals LP

Wilmington, DE 19850

Revised: March 2015

PACKAGE/LABEL PRINCIPAL DISPLAY PANEL – 1.5 mL pen-injector

SymlinPen® 60

(pramlintide acetate)

pen-injector

For Single Patient Use Only

For doses of 15 mcg, 30 mcg, 45 mcg, and 60 mcg.

Two disposable multidose pen-injectors pramlintide acetate 1000 mcg/mL, 1.5 mL

Subcutaneous use only. Pen needles not included. Use 29, 30, or 31 gauge disposable pen needles. Ask your healthcare provider which needle gauge and length is best for you.

Rx Only AstraZeneca

PACKAGE/LABEL PRINCIPAL DISPLAY PANEL – 2.7 mL pen-injector

SymlinPen® 120

(pramlintide acetate)

pen-injector

Two 2.7 mL disposable multidose pen-injectors 60•120 mcg NDC 0310-6627-02

For Single Patient Use Only

For doses of 60 mcg and 120 mcg.

Two disposable multidose pen-injectors pramlintide acetate 1000 mcg/mL, 2.7 mL

Subcutaneous use only. Pen needles not included. Use 29, 30, or 31 gauge disposable pen needles. Ask your healthcare provider which needle gauge and length is best for you.

Rx Only AstraZeneca